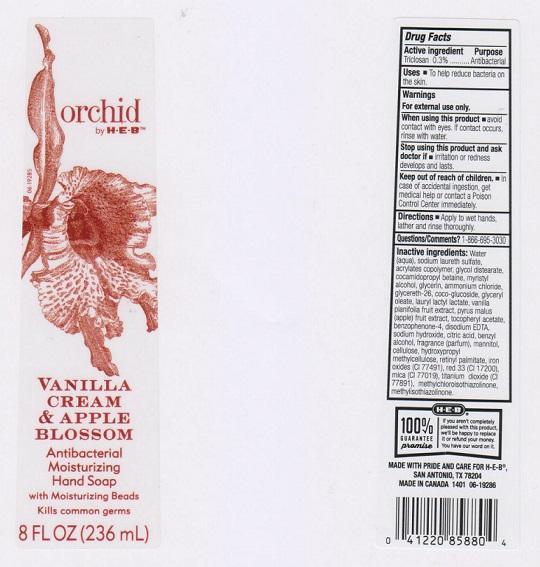 DRUG LABEL: ORCHID BY H E B
NDC: 37808-071 | Form: LIQUID
Manufacturer: H E B
Category: otc | Type: HUMAN OTC DRUG LABEL
Date: 20150119

ACTIVE INGREDIENTS: TRICLOSAN 3 mg/1 mL
INACTIVE INGREDIENTS: WATER; SODIUM LAURETH SULFATE; METHACRYLIC ACID - METHYL METHACRYLATE COPOLYMER (1:1); GLYCOL DISTEARATE; COCAMIDOPROPYL BETAINE; MYRISTYL ALCOHOL; GLYCERIN; AMMONIUM CHLORIDE; GLYCERETH-26; COCO GLUCOSIDE; GLYCERYL OLEATE; LAURYL LACTATE; VANILLA; APPLE; .ALPHA.-TOCOPHEROL ACETATE; SULISOBENZONE; EDETATE DISODIUM; SODIUM HYDROXIDE; CITRIC ACID MONOHYDRATE; BENZYL ALCOHOL; MANNITOL; POWDERED CELLULOSE; HYPROMELLOSES; VITAMIN A PALMITATE; FERRIC OXIDE RED; D&C RED NO. 33; MICA; TITANIUM DIOXIDE; METHYLCHLOROISOTHIAZOLINONE; METHYLISOTHIAZOLINONE

DRUG FACTS

ACTIVE INGREDIENT

TRICLOSAN 0.3%

PURPOSE

ANTIBACTERIAL

USES

TO HELP REDUCE BACTERIA ON THE SKIN

WARNINGS

FOR EXTERNAL USE ONLY

WHEN USING THIS PRODUCT

AVOID CONTACT WITH EYES. IF CONTACT OCCURS, RINSE WITH WATER

STOP USING THIS PRODUCT AND ASK DOCTOR IF

IRRITATION OR REDNESS DEVELOPS AND LASTS

KEEP OUT OF REACH OF CHILDREN

IN CASE OF ACCIDENTAL INGESTION, GET MEDICAL HELP OR CONTACT A POISON CONTROL CENTER IMMEDIATELY

DIRECTIONS

APPLY TO WET HANDS, LATHER AND RINSE THOROUGHLY

QUESTIONS/COMMENTS?

1-866-695-3030

INACTIVE INGREDIENTS

WATER (AQUA), SODIUM LAURETH SULFATE, ACRYLATES COPOLYMER, GLYCOL DISTEARATE, COCAMIDOPROPYL BETAINE, MYRISTYL ALCOHOL, GLYCERIN, AMMONIUM CHLORIDE, GLYCERETH-26, COCO-GLUCOSIDE, GLYCERYL OLEATE, LAURYL LACTYL LACTATE, VANILL PLANIFOLIA FRUIT EXTRACT, PYRUS MALUS (APPLE) FRUIT EXTRACT, TOCOPHERYL ACETATE, BENZOPHENONE-4, DISODIUM EDTA, SODIUM HYDROXIDE, CITRIC ACID, BENZYL ALCOHOL, FRAGRANCE (PARFUM), MANNITOL, CELLULOSE, HYDROYXPROPYL METHYLCELLULOSE, RETINYL PALMITATE, IRON OXIDES (CI 77491), RED 33 (CI 17200), MICA (CI 77019), TITANIUM DIOXIDE (CI 77891), METHYLCHLOROISOTHIAZOLINONE, METHYLISOTHIAZOLINONE